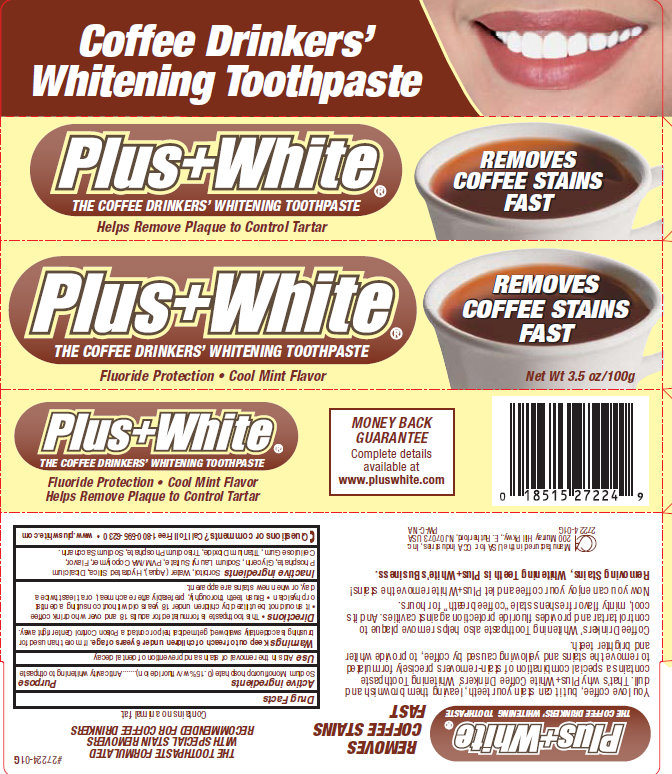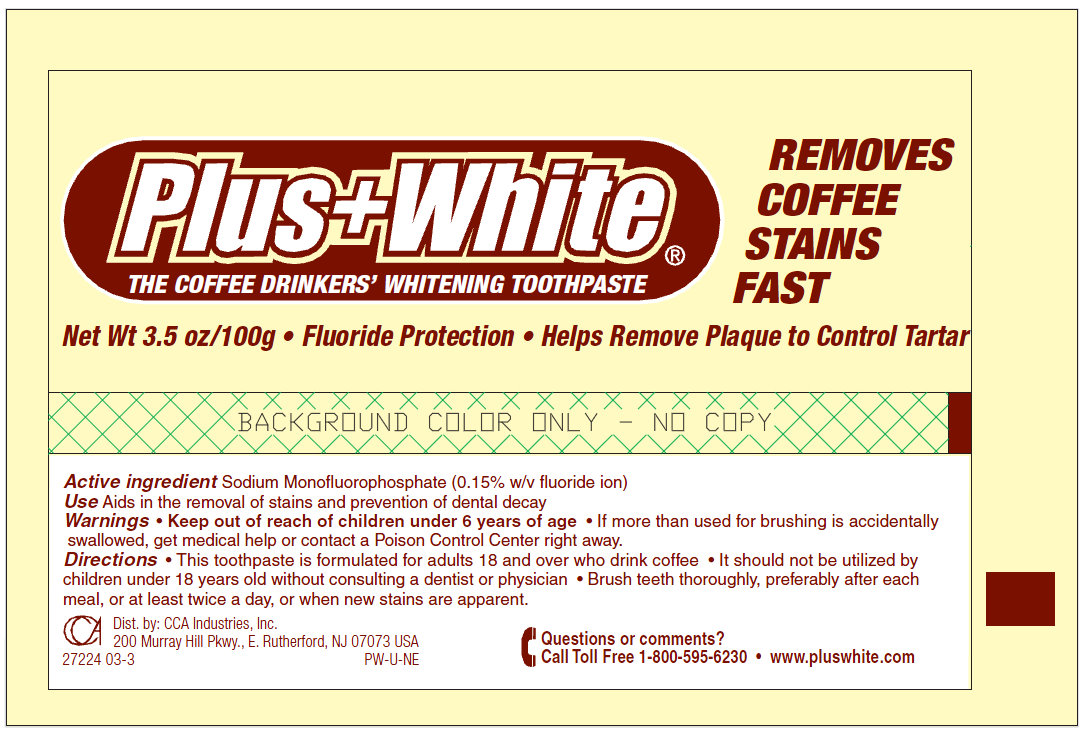 DRUG LABEL: Plus White Coffee Drinkers Whitening
NDC: 61543-7224 | Form: PASTE
Manufacturer: CCA Industries, Inc.
Category: otc | Type: HUMAN OTC DRUG LABEL
Date: 20200923

ACTIVE INGREDIENTS: SODIUM MONOFLUOROPHOSPHATE 1.5 mg/1 g
INACTIVE INGREDIENTS: SORBITOL; WATER; HYDRATED SILICA; ANHYDROUS DIBASIC CALCIUM PHOSPHATE; GLYCERIN; SODIUM LAURYL SULFATE; CARBOXYMETHYLCELLULOSE SODIUM; TITANIUM DIOXIDE; SACCHARIN SODIUM

Plus White Coffee Drinkers Whitening

Active ingredients

Sodium Monofluorophosphate (0.15% w/v fluoride ion)

Purpose

Anticavity whitening toothpaste

Use

Aids in the removal of stains and prevention of dental decay.

Warnings

under 6 years of age. If more than used for brushing is accidentally swallowed, get medical help or contact a Poison Control Center right away.

Keep out of reach of children

under 6 years of age. If more than used for brushing is accidentally swallowed, get medical help or contact a Poison Control Center right away.

Directions

- This toothpaste is formulated for adults 18 and over who drink coffee - It should not be utilized by children under 18 years old without consulting a dentist or physician
- Brush teeth thoroughly, preferably after each meal, or at least twice a day, or when new stains are apparent.

Inactive ingredients

Sorbitol, Water (Aqua), Hydrated Silica, Dicalcium Phosphate, Glycerin, Sodium Lauryl Sulfate, PVM/MA Copolymer, Flavor, Cellulose Gum, Titanium Dioxide, Trisodium Phosphate, Sodium Saccharin.

Questions or comments?

Call Toll Free1-800-595-6230 - www.pluswhite.com